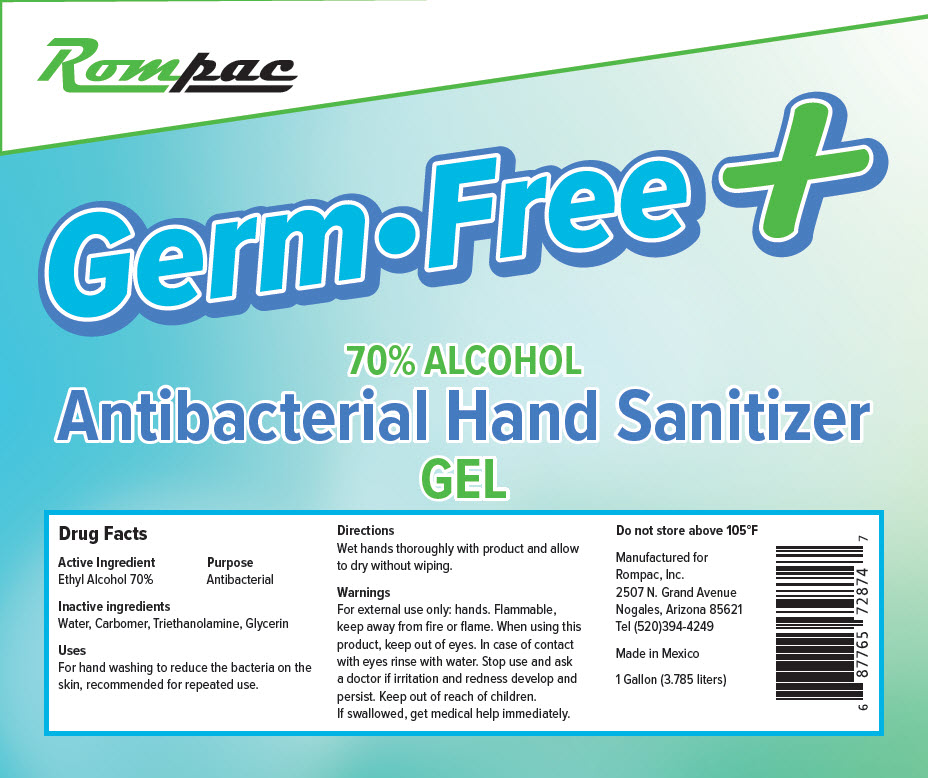 DRUG LABEL: Germ Free Plus Antibacterial Hand Sanitizer
NDC: 79357-001 | Form: GEL
Manufacturer: Rompac, Inc.
Category: otc | Type: HUMAN OTC DRUG LABEL
Date: 20200715

ACTIVE INGREDIENTS: Alcohol 70 mL/100 mL
INACTIVE INGREDIENTS: WATER; CARBOMER HOMOPOLYMER, UNSPECIFIED TYPE; Triethanolamine Lactate; GLYCERIN

Germ Free + Antibacterial Hand Sanitizer

Drug Facts

Active Ingredient

Ethyl Alcohol 70%

Purpose

Antibacterial

Inactive ingredients

Water, Carbomer, Triethanolamine, Glycerin

Uses

For hand washing to reduce the bacteria on the skin, recommended for repeated use.

Directions

Wet hands thoroughly with product and allow to dry without wiping.

Warnings

For external use only: hands. Flammable, keep away from fire or flame. When using this product, keep out of eyes. In case of contact with eyes rinse with water. Stop use and ask a doctor if irritation and redness develop and persist.

Keep out of reach of children.

If swallowed, get medical help immediately.

STORAGE AND HANDLING

Do not store above 105°F

PRINCIPAL DISPLAY PANEL - 1 Gallon Bottle Label

Rompac

Germ•Free +

70% ALCOHOL
Antibacterial Hand Sanitizer
GEL

1 Gallon (3.785 liters)